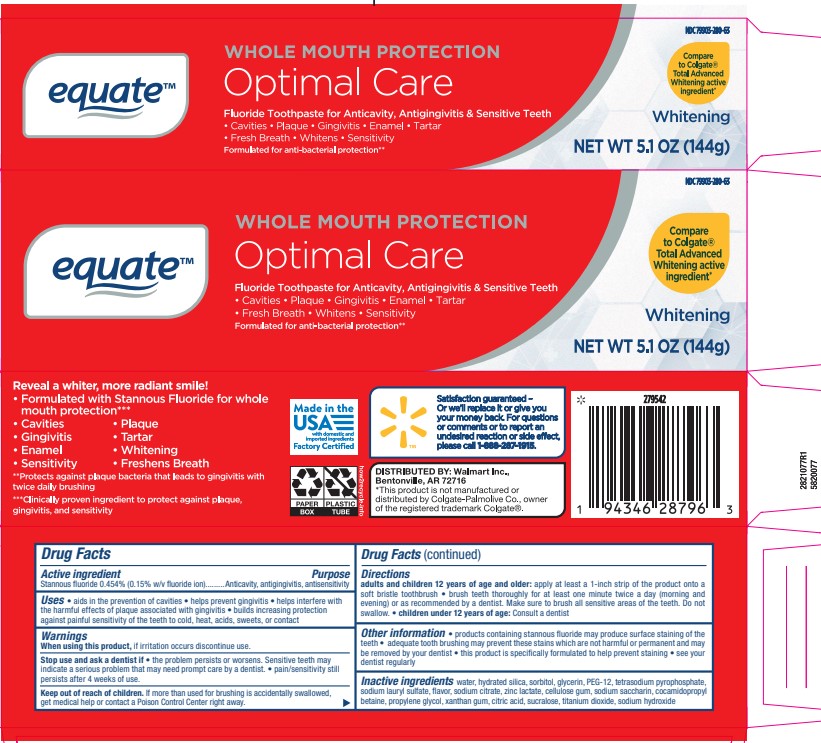 DRUG LABEL: Equate Optimal Care TP
NDC: 79903-280 | Form: PASTE, DENTIFRICE
Manufacturer: Walmart Inc.
Category: otc | Type: HUMAN OTC DRUG LABEL
Date: 20251113

ACTIVE INGREDIENTS: STANNOUS FLUORIDE 0.16 g/100 g
INACTIVE INGREDIENTS: PROPYLENE GLYCOL; HYDRATED SILICA; POLYETHYLENE GLYCOL 12000; SODIUM HYDROXIDE; XANTHAN GUM; SACCHARIN SODIUM; ANHYDROUS TRISODIUM CITRATE; GLYCERIN; ANHYDROUS CITRIC ACID; TITANIUM DIOXIDE; SODIUM LAURYL SULFATE; SODIUM PYROPHOSPHATE; CARBOXYMETHYLCELLULOSE SODIUM; SUCRALOSE; SORBITOL; COCAMIDOPROPYL BETAINE; WATER; ZINC LACTATE

5820077 Walmart Equate Optimal Care (80-15077)

ACTIVE INGREDIENT

Stannous fluoride 0.454% (0.15% w/v fluoride ion)

INACTIVE INGREDIENT

water, hydrated silica, sorbitol, glycerin, PEG-12, tetrasodium pyrophosphate, sodium lauryl sulfate, flavor, sodium citrate, zinc lactate, cellulose gum, sodium saccharin, cocamidopropyl betaine, propylene glycol, xanthan gum, citric acid, sucralose, titanium dioxide, sodium hydroxide

PURPOSE

Anticavity, antigingivitis, antisensitivity

INDICATIONS AND USAGE

aids in the prevention of cavities

helps prevent gingivitis

helps interfere with the harmful effects of plaque associated with gingivitis

builds increasing protection against painful sensitivity of the teeth to cold, heat, acids, sweets, or contact

When using this product, if irritation occurs discontinue use.

Stop use and ask a dentist if • the problem persists or worsens. Sensitive teeth may indicate a serious problem that may need prompt care by a dentist. • pain/sensitivity still persists after 4 weeks of use.

Keep out of reach of children. If more than used for brushing is accidentally swallowed, get medical help or contact a Poison Control Center right away.

DOSAGE AND ADMINISTRATION

Directions adults and children 12 years of age and older: apply at least a 1-inch strip of the product onto a soft bristle toothbrush • brush teeth thoroughly for at least one minute twice a day (morning and evening) or as recommended by a dentist.

Make sure to brush all sensitive areas of the teeth. Do not swallow. • children under 12 years of age: Consult a dentist